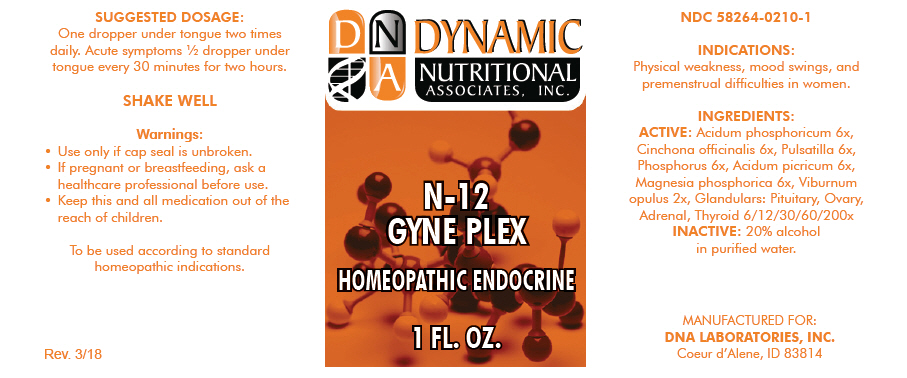 DRUG LABEL: N-12
NDC: 58264-0210 | Form: SOLUTION
Manufacturer: DNA Labs, Inc.
Category: homeopathic | Type: HUMAN OTC DRUG LABEL
Date: 20250109

ACTIVE INGREDIENTS: PHOSPHORIC ACID 6 [hp_X]/1 mL; CINCHONA OFFICINALIS BARK 6 [hp_X]/1 mL; ANEMONE PULSATILLA 6 [hp_X]/1 mL; PHOSPHORUS 6 [hp_X]/1 mL; PICRIC ACID 6 [hp_X]/1 mL; MAGNESIUM PHOSPHATE, DIBASIC TRIHYDRATE 6 [hp_X]/1 mL; VIBURNUM OPULUS WHOLE 2 [hp_X]/1 mL; BOS TAURUS PITUITARY GLAND, POSTERIOR 200 [hp_X]/1 mL; BOS TAURUS OVARY 200 [hp_X]/1 mL; BOS TAURUS ADRENAL GLAND 200 [hp_X]/1 mL; THYROID, UNSPECIFIED 200 [hp_X]/1 mL
INACTIVE INGREDIENTS: ALCOHOL; WATER

N-12

NDC 58264-0210-1

INDICATIONS

PURPOSE

Physical weakness, mood swings, and premenstrual difficulties in women.

INGREDIENTS

ACTIVE

Acidum phosphoricum 6x, Cinchona officinalis 6x, Pulsatilla 6x, Phosphorus 6x, Acidum picricum 6x, Magnesia phosphorica 6x, Viburnum opulus 2x, Glandulars: Pituitary, Ovary, Adrenal, Thyroid 6/12/30/60/200x

INACTIVE

20% alcohol in purified water.

SUGGESTED DOSAGE

One dropper under tongue two times daily. Acute symptoms ½ dropper under tongue every 30 minutes for two hours.

STORAGE AND HANDLING

SHAKE WELL

Warnings

- Use only if cap seal is unbroken.

PREGNANCY OR BREAST FEEDING

- If pregnant or breastfeeding, ask a healthcare professional before use.

KEEP OUT OF REACH OF CHILDREN

- Keep this and all medication out of the reach of children.

To be used according to standard homeopathic indications.

PRINCIPAL DISPLAY PANEL - 1 FL. OZ. Bottle Label

DYNAMIC
NUTRITIONAL
ASSOCIATES, INC.

N-12
GYNE PLEX

HOMEOPATHIC ENDOCRINE

1 FL. OZ.